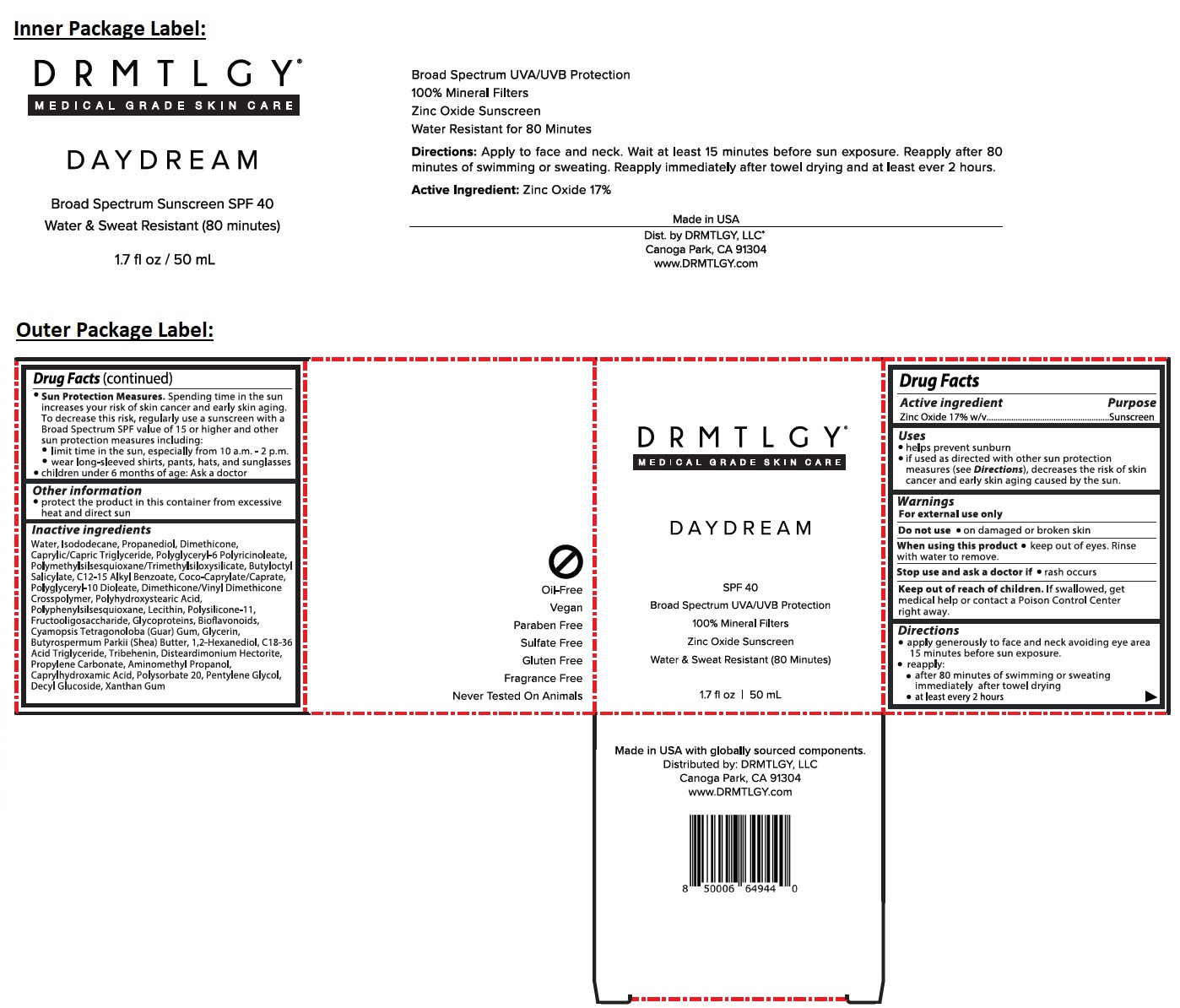 DRUG LABEL: DAYDREAM Broad Spectrum Sunscreen SPF 40
NDC: 83286-001 | Form: CREAM
Manufacturer: Drmtlgy, LLC
Category: otc | Type: HUMAN OTC DRUG LABEL
Date: 20251118

ACTIVE INGREDIENTS: ZINC OXIDE 17 g/100 mL
INACTIVE INGREDIENTS: WATER; ISODODECANE; PROPANEDIOL; DIMETHICONE, UNSPECIFIED; MEDIUM-CHAIN TRIGLYCERIDES; POLYGLYCERYL-6 POLYRICINOLEATE; POLYMETHYLSILSESQUIOXANE/TRIMETHYLSILOXYSILICATE; BUTYLOCTYL SALICYLATE; ALKYL (C12-15) BENZOATE; COCOYL CAPRYLOCAPRATE; POLYGLYCERYL-10 DIOLEATE; DIMETHICONE/VINYL DIMETHICONE CROSSPOLYMER (HARD PARTICLE); POLYHYDROXYSTEARIC ACID (2300 MW); PHENYLSILANETRIOL; SOYBEAN LECITHIN; DIMETHICONE/VINYL DIMETHICONE CROSSPOLYMER (SOFT PARTICLE); SACCHARUM OFFICINARUM STEM FRUCTOOLIGOSACCHARIDES; PLATELET GLYCOPROTEIN VI; CITRUS BIOFLAVONOIDS; GUAR GUM; GLYCERIN; SHEA BUTTER; 1,2-HEXANEDIOL; C18-36 ACID TRIGLYCERIDE; TRIBEHENIN; DISTEARDIMONIUM HECTORITE; PROPYLENE CARBONATE; AMINOMETHYLPROPANOL; CAPRYLHYDROXAMIC ACID; POLYSORBATE 20; PENTYLENE GLYCOL; DECYL GLUCOSIDE; XANTHAN GUM

DRMTLGY® DAYDREAM Broad Spectrum SPF 40 Sunscreen

Active ingredient

Zinc Oxide 17% w/v

Purpose

Sunscreen

Uses

• helps prevent sunburn
• if used as directed with other sun protection measures (see Directions), decreases the risk of skin cancer and early skin aging caused by the sun.

Warnings

For external use only

Do not use • on damaged or broken skin

When using this product • keep out of eyes. Rinse with water to remove.

Stop use and ask a doctor if • rash occurs

Keep out of reach of children. If swallowed, get medical help or contact a Poison Control Center right away.

Directions

• apply generously to face and neck avoiding eye area 15 minutes before sun exposure.
• reapply:
• after 80 minutes of swimming or sweating
immediately after towel drying
• at least every 2 hours
• Sun Protection Measures. Spending time in the sun increases your risk of skin cancer and early skin aging. To decrease this risk, regularly use a sunscreen with a Broad Spectrum SPF value of 15 or higher and other sun protection measures including:
• limit time in the sun, especially from 10 a.m. - 2 p.m.
• wear long-sleeved shirts, pants, hats, and sunglasses
• children under 6 months of age: Ask a doctor

Other information

• protect the product in this container from excessive heat and direct sun

Inactive ingredients

Water, Isododecane, Propanediol, Dimethicone, Caprylic/Capric Triglyceride, Polyglyceryl-6 Polyricinoleate, Polymethylsilsesquioxane/Trimethylsiloxysilicate, Butyloctyl Salicylate, C12-15 Alkyl Benzoate, Coco-Caprylate/Caprate, Polyglyceryl-10 Dioleate, Dimethicone/Vinyl Dimethicone Crosspolymer, Polyhydroxystearic Acid, Polyphenylsilsesquioxane, Lecithin, Polysilicone-11, Fructooligosaccharide, Glycoproteins, Bioflavonoids, Cyamopsis Tetragonoloba (Guar) Gum, Glycerin, Butyrospermum Parkii (Shea) Butter, 1,2-Hexanediol, C18-36 Acid Triglyceride, Tribehenin, Disteardimonium Hectorite, Propylene Carbonate, Aminomethyl Propanol, Caprylhydroxamic Acid, Polysorbate 20, Pentylene Glycol, Decyl Glucoside, Xanthan Gum

MEDICAL GRADE SKIN CARE

UVA/UVB Protection

100% Mineral Filters

Water & Sweat Resistant (80 Minutes)

Oil-Free

Vegan

Paraben Free

Sulfate Free

Gluten Free

Fragrance Free

Never Tested On Animals

Made in USA with globally sourced components.
Distributed by: DRMTLGY, LLC
Canoga Park, CA 91304
www.DRMTLGY.com